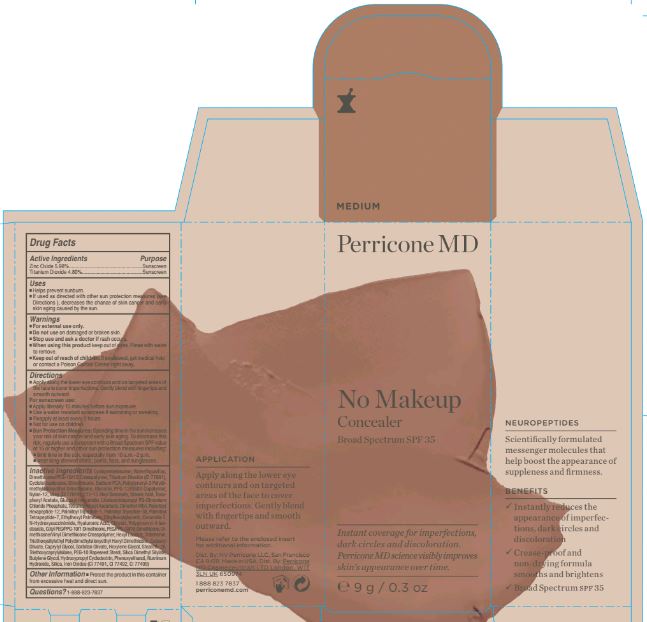 DRUG LABEL: No Makeup Concealer Medium Broad Spectrum SPF 35
NDC: 62742-4106 | Form: CREAM
Manufacturer: Allure Labs, Inc
Category: otc | Type: HUMAN OTC DRUG LABEL
Date: 20171201

ACTIVE INGREDIENTS: ZINC OXIDE 59.8 mg/1 g; TITANIUM DIOXIDE 48.0 mg/1 g
INACTIVE INGREDIENTS: CYCLOMETHICONE 5; WATER; CYCLOMETHICONE 4; DIMETHICONE; SODIUM PYRROLIDONE CARBOXYLATE; POLYGLYCERYL-3 POLYDIMETHYLSILOXYETHYL DIMETHICONE (4000 MPA.S); GLYCERIN; PPG-12/SMDI COPOLYMER; NYLON-12; MICA; ALKYL (C12-15) BENZOATE; STEARIC ACID; .ALPHA.-TOCOPHEROL ACETATE; GLUCOSYL HESPERIDIN; LINOLEAMIDOPROPYL PG-DIMONIUM CHLORIDE PHOSPHATE; TETRAHEXYLDECYL ASCORBATE; DEANOL; PALMITOYL HEXAPEPTIDE-12; PALMITOYL LYSYLDIOXYMETHIONYLLYSINE; PALMITOYL TETRAPEPTIDE-7; ETHYLHEXYL PALMITATE; ETHYLHEXYLGLYCERIN; CERAMIDE 2; N-HYDROXYSUCCINIMIDE; HYALURONIC ACID; CHRYSIN; POLYGLYCERYL-4 ISOSTEARATE; CETYL PEG/PPG-10/1 DIMETHICONE (HLB 1.5); PEG/PPG-18/18 DIMETHICONE; DIMETHICONE/VINYL DIMETHICONE CROSSPOLYMER (SOFT PARTICLE); HEXYL LAURATE; TRIBEHENIN; CETEARYL OLIVATE; CAPRYLYL GLYCOL; SORBITAN OLIVATE; HEXYLENE GLYCOL; STEARETH-20; PEG-10 RAPESEED STEROL; TRIETHOXYCAPRYLYLSILANE; SILICA DIMETHYL SILYLATE; BUTYLENE GLYCOL; HYDROXYPROPYL .ALPHA.-CYCLODEXTRIN; Phenoxyethanol; ALUMINUM HYDROXIDE; SILICON DIOXIDE; FERRIC OXIDE RED; FERRIC OXIDE YELLOW; FERROSOFERRIC OXIDE; PALMITOYL TRIPEPTIDE-1

Drug Facts

Active Ingredients:

Zinc Oxide - 5.98%

Titanium Dioxide - 4.80%

PURPOSE

Sunscreen

INDICATIONS AND USAGE

Helps prevent sunburn.

if used as directed with other sun protection measures (see directions), decreases the chance of skin cancer and early skin aging casued by the sun.

WARNINGS

For external use only.

Do not use:

on damaged or broken skin.

Stop use and ask a doctor if rash occurs.

WHEN USING

keep out of eyes. rinse with water to remove.

KEEP OUT OF REACH OF CHILDREN

if swallowed, get medical help or contact a Poison Control Center right away.

DOSAGE AND ADMINISTRATION

Directions: Apply along the lower eye contours. genty blend with fingertips and smooth outward. Any excess can also be applied on targeted areas of the face to cover imperfections.

For sunscreen use: apply liberally 15 minutes before sun exposure. use a water resistant sunscreen if swimming or sweating. reapply at atleast every 2 hours. not for use on children.

Sun protection measures: Spending time in the sun increases your risk of skin cancer and early skin aging. to decrease the risk, regularly use a sunscreen with a Broad Spectrum SPF value of 15 or higher and other sun protection measures including limit time in the sun, especially from 10 a.m. - 2 p.m. wear long sleeved shirts, pants, hats, and sunglasses.

INACTIVE INGREDIENT

Inactive Ingredients: Cyclopentasiloxane, Water/Aqua/Eau, Dimethicone/PEG-10/15 Crosspolymer, Cyclotetrasiloxane, Dimethicone, Sodium PCA, Polyglyceryl-3 polydimethylsiloxylethyl Dimethicone, glycerin, PPG-12/SMDI Copolymer, Nylon-12, Mica (CI 77019), C12-15 Alkyl Benzoate, Stearic Acid, Tocopheryl Acetate, Glucosyl Hespeidin, Linoleamidopropyl PG-Dimonium Chloride Phosphate, tetrahexyldecyl Ascorbate, Dimethyl MEA, Palmitoyl Hexapeptide, Palmitoyl Tripeptide-1, Palmitoyl Tripeptide-38, Palmitoyl Tetrapeptide-7, Ethylhexyl Palmitate, Ethyhexylglycerin, Ceremide 2, N-Hydroxysuccinimide, Hyaluronic Acid, Chrysin, Polyglyceryl-4 Isostearate, Cetyl PEG/PPG-10/1 Dimethicone, PEG/PPG-18/18 Dimethicone, Dimethicone/Vimyl Dimethicone Crosspolymer, Hexyl Laurate, Tribehenin, Triethoxysilylethyl Polydimethylsiloxylethyl Hexyl Dimethicone, Ceteary Olivate, Caprylyl Glycol, Sorbitan Olivate, Hexylene Glycol, Steareth-20, PEG-10 Rapeseed Sterol, Triethoxycaprylylsilane, Silica Dimethyl Silylate, Butylene Glycol, Hydroxypropyl Cyclodextrin, phenoxyethanol, Aluminum Hydroxide, Silica, Iron oxides (CI 77491, CI77492, CI 77499).

PACKAGE LABEL

Dist By: NV Perricone LLC

San Francisco, CA 94111

Madse in USA

1 888 823 7837

perriconemd.com